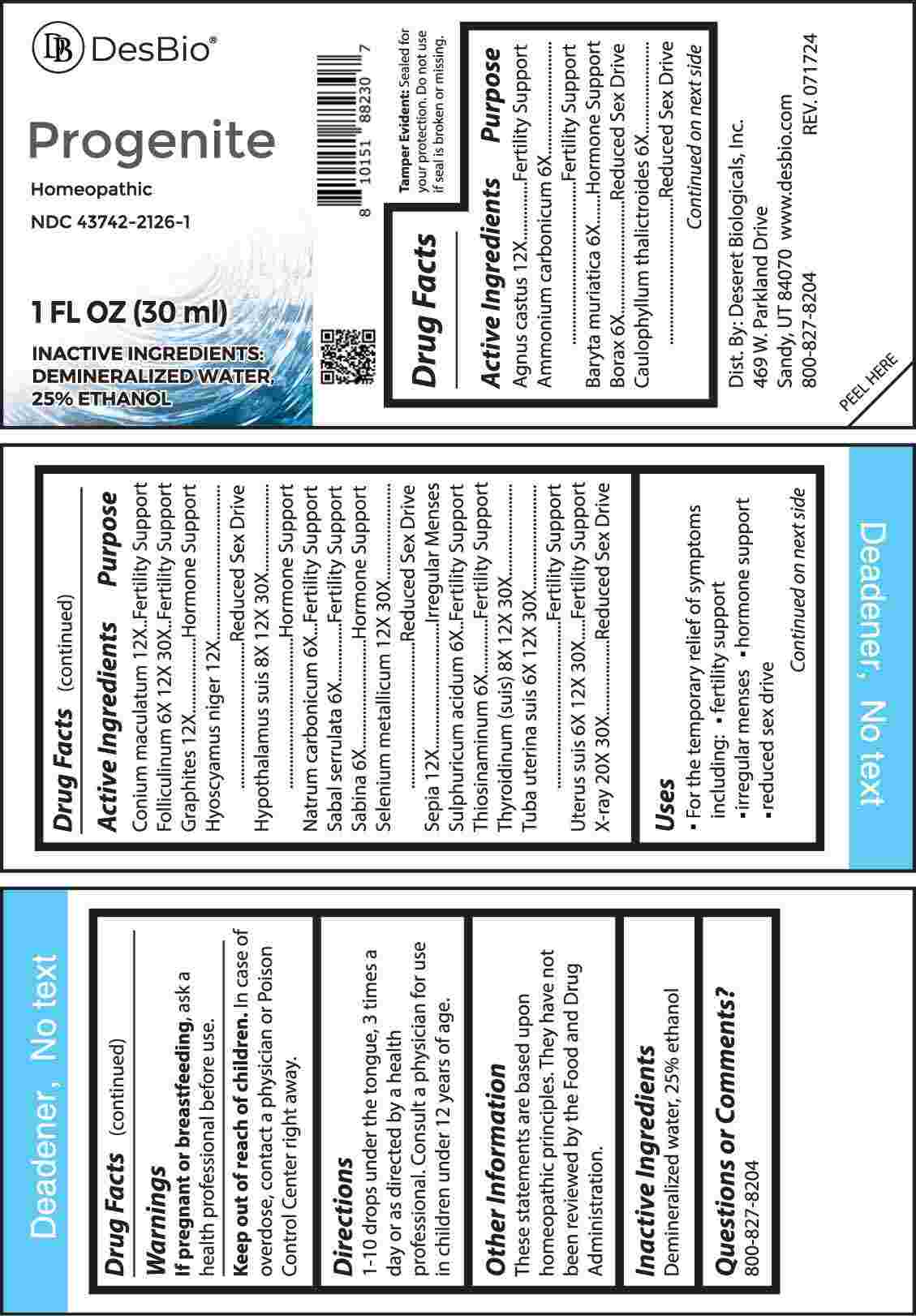 DRUG LABEL: Progenite
NDC: 43742-2126 | Form: LIQUID
Manufacturer: Deseret Biologicals
Category: homeopathic | Type: HUMAN OTC DRUG LABEL
Date: 20241023

ACTIVE INGREDIENTS: AMMONIUM CARBONATE 6 [hp_X]/1 mL; BARIUM CHLORIDE DIHYDRATE 6 [hp_X]/1 mL; SODIUM BORATE 6 [hp_X]/1 mL; CAULOPHYLLUM THALICTROIDES ROOT 6 [hp_X]/1 mL; SODIUM CARBONATE 6 [hp_X]/1 mL; SAW PALMETTO 6 [hp_X]/1 mL; JUNIPERUS SABINA LEAFY TWIG 6 [hp_X]/1 mL; SULFURIC ACID 6 [hp_X]/1 mL; ALLYLTHIOUREA 6 [hp_X]/1 mL; ESTRONE 6 [hp_X]/1 mL; SUS SCROFA FALLOPIAN TUBE 6 [hp_X]/1 mL; SUS SCROFA UTERUS 6 [hp_X]/1 mL; SUS SCROFA HYPOTHALAMUS 8 [hp_X]/1 mL; THYROID 8 [hp_X]/1 mL; CHASTE TREE FRUIT 12 [hp_X]/1 mL; CONIUM MACULATUM FLOWERING TOP 12 [hp_X]/1 mL; GRAPHITE 12 [hp_X]/1 mL; HYOSCYAMUS NIGER 12 [hp_X]/1 mL; SEPIA OFFICINALIS JUICE 12 [hp_X]/1 mL; SELENIUM 12 [hp_X]/1 mL; ALCOHOL, X-RAY EXPOSED (1000 RAD) 20 [hp_X]/1 mL
INACTIVE INGREDIENTS: WATER; ALCOHOL

DRUG FACTS:

ACTIVE INGREDIENTS:

Agnus Castus 12X, Ammonium Carbonicum 6X, Baryta Muriatica 6X, Borax 6X, Caulophyllum Thalictroides 6X, Conium Maculatum 12X, Folliculinum 6X, 12X, 30X, Graphites 12X, Hyoscyamus Niger 12X, Hypothalamus Suis 8X, 12X, 30X, Natrum Carbonicum 6X, Sabal Serrulata 6X, Sabina 6X, Selenium Metallicum 12X, 30X, Sepia 12X, Sulphuricum Acidum 6X, Thiosinaminum 6X, Thyroidinum (Suis) 8X, 12X, 30X, Tuba Uterina Suis 6X, 12X, 30X, Uterus Suis 6X, 12X, 30X, X-Ray 20X, 30X.

PURPOSE:

Agnus Castus – Fertility Support, Ammonium Carbonicum – Fertility Support, Baryta Muriatica – Hormone Support, Borax – Reduced Sex Drive, Caulophyllum Thalictroides – Reduced Sex Drive, Conium Maculatum – Fertility Support, Folliculinum – Fertility Support, Graphites – Hormone Support, Hyoscyamus Niger – Reduced Sex Drive, Hypothalamus Suis – Hormone Support, Natrum Carbonicum – Fertility Support, Sabal Serrulata – Fertility Support, Sabina – Hormone Support, Selenium Metallicum – Reduced Sex Drive, Sepia – Irregular Menses, Sulphuricum Acidum – Fertility Support, Thiosinaminum – Fertility Support, Thyroidinum (Suis) - Hormone Support, Tuba Uterina Suis – Fertility Support, Uterus Suis – Fertility Support, X-Ray – Reduced Sex Drive

USES:

• For the temporary relief of symptoms including:

• fertility support • irregular menses • hormonal support • reduced sex drive
These statements are based upon homeopathic principles. They have not been reviewed by the Food and Drug Administration.

WARNINGS:

If pregnant or breast-feeding, ask a health professional before use.

Keep out of reach of children. In case of overdose, contact a physician or Poison Control Center right away.

Tamper Evident: Sealed for your protection. Do not use if seal is broken or missing.

KEEP OUT OF REACH OF CHILDREN:

In case of overdose, contact a physician or Poison Control Center right away.

DIRECTIONS:

1-10 drops under the tongue, 3 times a day or as directed by a health professional. Consult a physician for use in children under 12 years of age.

INACTIVE INGREDIENTS:

Demineralized water, 25% ethanol

QUESTIONS:

Dist. By: Deseret Biologicals, Inc.
469 W. Parkland Drive
Sandy, UT 84070

www.desbio.com

800-

PACKAGE LABEL DISPLAY:

DesBio

Progenite

Homeopathic
NDC 43742-2126-1
1 FL OZ (30 ml)